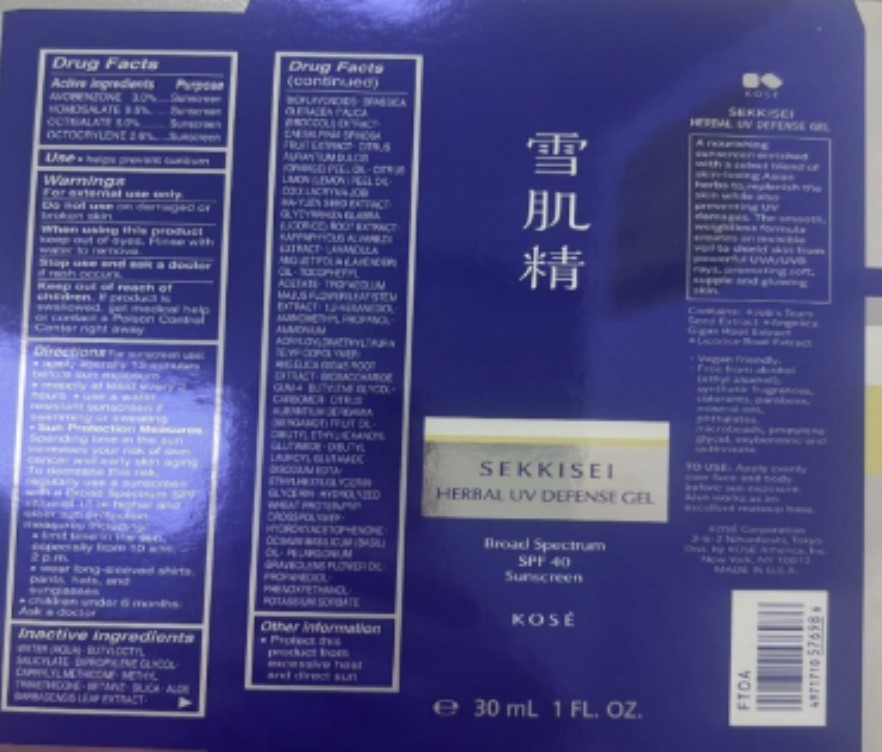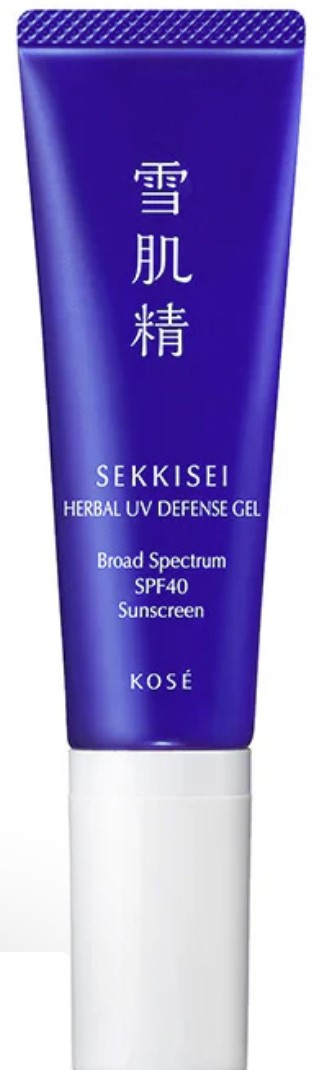 DRUG LABEL: HERBAL UV DEFENSE SPF40
NDC: 68577-199 | Form: GEL
Manufacturer: COSMAX USA, CORPORATION
Category: otc | Type: HUMAN OTC DRUG LABEL
Date: 20241230

ACTIVE INGREDIENTS: HOMOSALATE 9.5 mg/100 mg; OCTISALATE 5 mg/100 mg; AVOBENZONE 3 mg/100 mg; OCTOCRYLENE 2.6 mg/100 mg
INACTIVE INGREDIENTS: METHYL TRIMETHICONE; BETAINE; SILICON DIOXIDE; GLYCERIN; CAESALPINIA SPINOSA FRUIT POD; ORANGE OIL, COLD PRESSED; .ALPHA.-TOCOPHEROL ACETATE; ALOE VERA LEAF; CITRUS BIOFLAVONOIDS; 1,2-HEXANEDIOL; HYDROLYZED WHEAT PROTEIN (ENZYMATIC, 3000 MW); AMMONIUM ACRYLOYLDIMETHYLTAURATE/VP COPOLYMER; KAPPAPHYCUS ALVAREZII; WATER; BUTYLOCTYL SALICYLATE; LAVENDER OIL; PHENOXYETHANOL; CAPRYLYL TRISILOXANE; BROCCOLI; TROPAEOLUM MAJUS FLOWERING TOP; DIBUTYL ETHYLHEXANOYL GLUTAMIDE; GLYCYRRHIZA GLABRA; BUTYLENE GLYCOL; ANGELICA GIGAS ROOT; HYDROXYACETOPHENONE; BASIL OIL; AMINOMETHYLPROPANOL; LEMON OIL, COLD PRESSED; EDETATE DISODIUM; COIX LACRYMA-JOBI VAR. MA-YUEN SEED; BIOSACCHARIDE GUM-4; DIBUTYL LAUROYL GLUTAMIDE; PELARGONIUM GRAVEOLENS FLOWER OIL; PROPANEDIOL; DIPROPYLENE GLYCOL; CARBOMER HOMOPOLYMER TYPE B (ALLYL PENTAERYTHRITOL OR ALLYL SUCROSE CROSSLINKED); POTASSIUM SORBATE

SEKKISEI HERBAL UV DEFENSE GEL BROAD SPECTRUM SPF40

Active Ingredients

Homosalate 9.5%

Octisalate 5%

Avobenzone 3.0%

Octocrylene 2.6%

Purpose

Sunscreen

USES

- Helps prevent sunburn

WARNINGS

For external use only.

Do not useon damaged or broken skin.

WHEN USING

When using this productkeep out of eyes. Rinse with water to remove

Stop use and ask a doctorif rash occurs.

Keep out of reach of children. If product is swallowed, get medical help or contact a Poison Control Center right away.

DIRECTIONS

- Apply liberally 15 minutes before sun exposure
- Use a water resistant sunscreen if swimming or sweating
- Reapply at least every 2 hours

• Sun Protection Measures.
Spending time in the sun increases your risk of skin cancer and early skin aging. To decrease this risk, regularly use a sunscreen with a Broad Spectrum SPF value of 15 or higher and other sun protection measures including:
• limit time in the sun, especially from 10 a.m. - 2 p.m.
• wear long-sleeved shirts, pants, hats, and sunglasses

- Children under 6 months: Ask a doctor

Inactive Ingredients

Water, Isoamyl Laurate, Glycerin, Caprylic/Capric Triglyceride, Butyloctyl Salicylate, Polyglyceryl-10 Stearate, Poly C10-30 Alkyl Acrylate, Polyhydroxystearic Acid, Hydroxyethyl Acrylate/Sodium Acryloyldimethyl Taurate Copolymer, Cetearyl Olivate, Sorbitan Olivate, Hydroxyacetoph-enone, Phenoxyethanol, Polyglyceryl-10 Laurate, Microcrystalline Cellulose, Limonene, Rubus Idaeus (Raspberry) Seed Oil, Xanthan Gum, Glycine Soja (Soybean) Oil, Cellulose Gum, Citrus Aurantium Bergamia (Bergamot) Fruit Oil, Polyglyceryl-3 Diisostearate, Citrus Limon (Lemon) Peel Oil, Linalool, Citrus Aurantium Dulcis (Orange) Peel Oil, Oryza Sativa (Rice) Extract, Oryza Sativa (Rice) Germ Extract, Lavandula Angustifolia (Lavender) Oil, Propanediol, Ocimum Basilicum (Basil) Oil, Pelargonium Graveolens Flower Oil, Citral, Centella Asiatica Extract

OTHER INFORMATION

Protect this product from excessive heat and direct sun